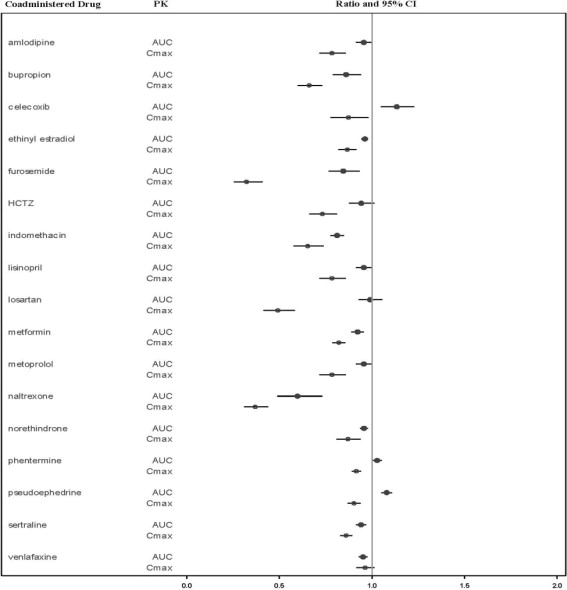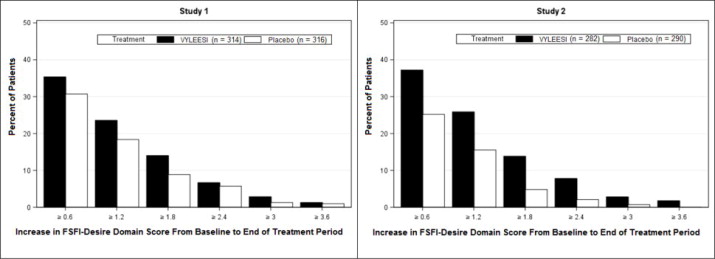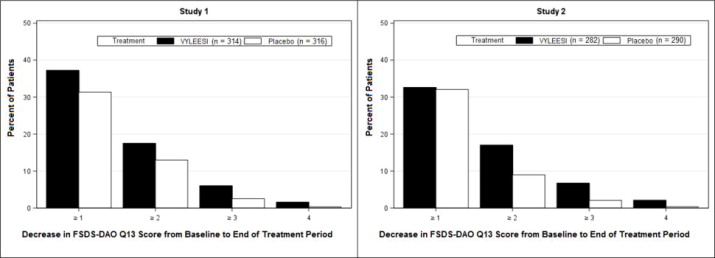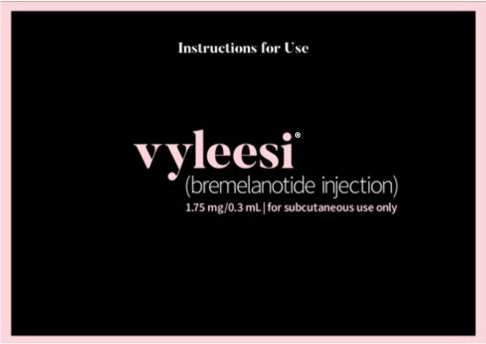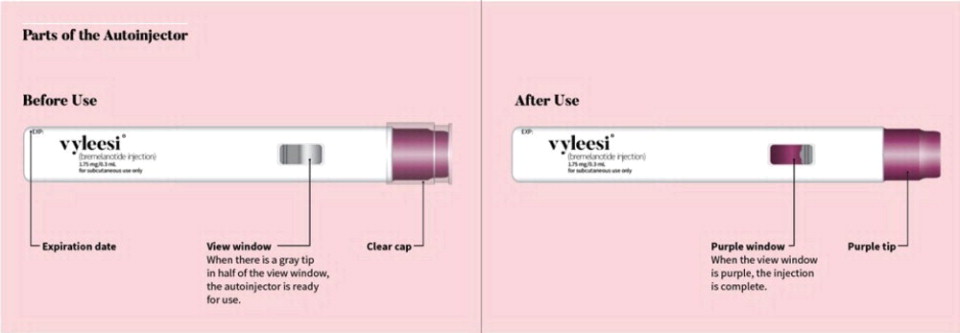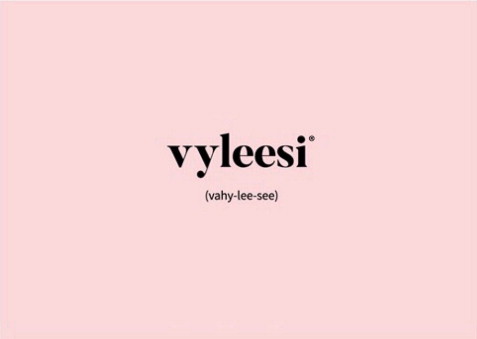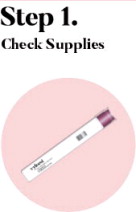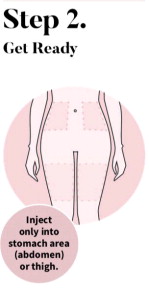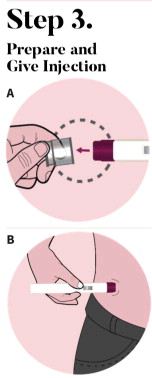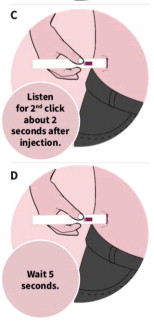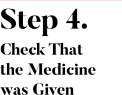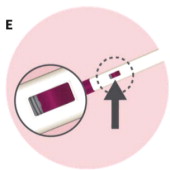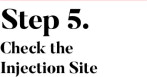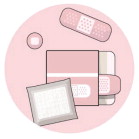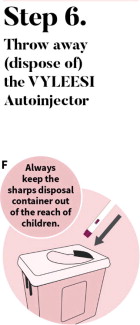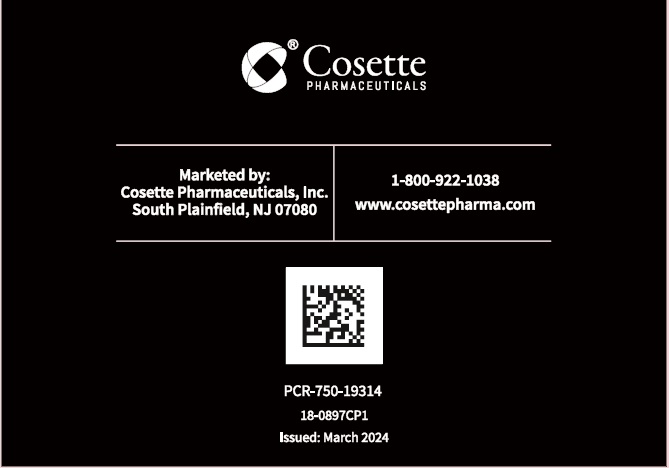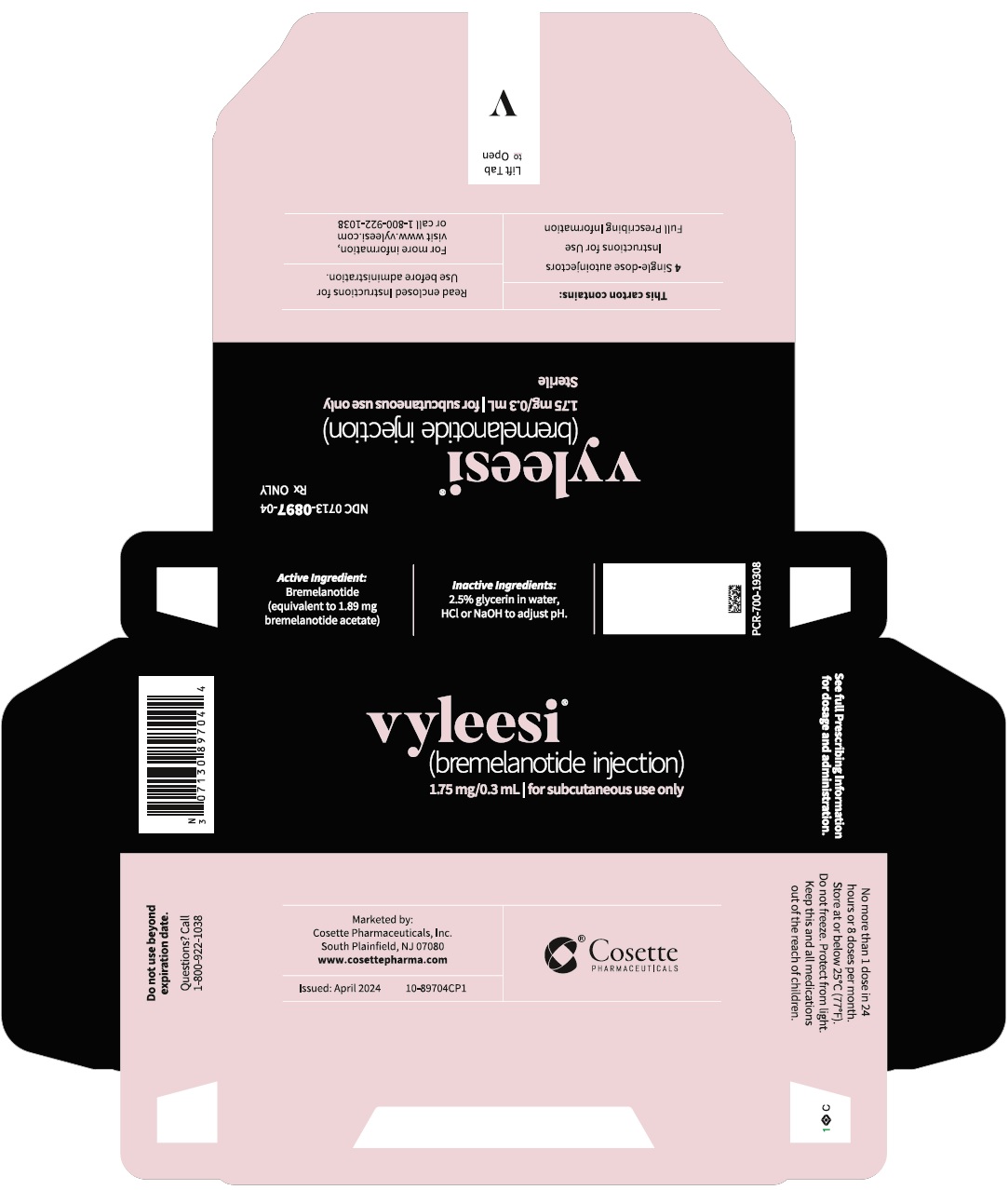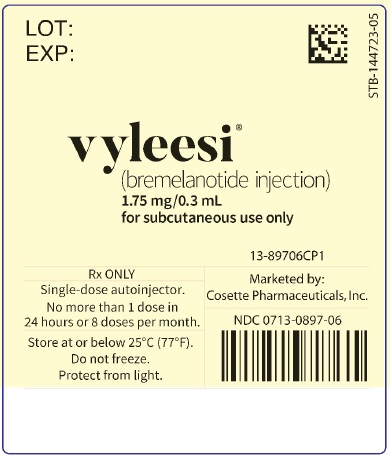 DRUG LABEL: Vyleesi
NDC: 0713-0897 | Form: INJECTION
Manufacturer: Cosette Pharmaceuticals, Inc.
Category: prescription | Type: HUMAN PRESCRIPTION DRUG LABEL
Date: 20251113

ACTIVE INGREDIENTS: BREMELANOTIDE ACETATE 1.75 mg/0.3 mL
INACTIVE INGREDIENTS: GLYCERIN; WATER; SODIUM HYDROXIDE; HYDROCHLORIC ACID

HIGHLIGHTS OF PRESCRIBING INFORMATION

These highlights do not include all the information needed to use VYLEESI® safely and effectively. See full prescribing information for VYLEESI
VYLEESI (bremelanotide injection), for subcutaneous use
Initial U.S. Approval: 2019

1 INDICATIONS AND USAGE

VYLEESI is a melanocortin receptor agonist indicated for the treatment of premenopausal women with acquired, generalized hypoactive sexual desire disorder (HSDD) as characterized by low sexual desire that causes marked distress or interpersonal difficulty and is NOT due to:

- A co-existing medical or psychiatric condition,
- Problems with the relationship, or
- The effects of a medication or drug substance (1).

Limitations of Use (1):

- Not indicated for treatment of HSDD in postmenopausal women or in men.
- Not indicated to enhance sexual performance.

2 DOSAGE AND ADMINISTRATION

- Inject 1.75 mg subcutaneously via the autoinjector to the abdomen or thigh, as needed, at least 45 minutes before anticipated sexual activity. (2.1)
- Do not administer more than one dose within 24 hours. (2.1)
- More than 8 doses per month is not recommended. (2.1)

3 DOSAGE FORMS AND STRENGTHS

Subcutaneous injection: 1.75 mg/0.3 mL solution. (3)

4 CONTRAINDICATIONS

Uncontrolled hypertension or known cardiovascular disease. (4)

5 WARNINGS AND PRECAUTIONS

- Transient increase in blood pressure and decrease in heart rate: Occurs after each dose and usually resolves within 12 hours. Consider the patient's cardiovascular risk before initiating VYLEESI and periodically during treatment and ensure blood pressure is well-controlled. VYLEESI is not recommended in patients at high risk for cardiovascular disease. (5.1)
- Focal hyperpigmentation: Reported by 1% of patients who received up to 8 doses per month, including involvement of the face, gingiva and breasts. Higher risk in patients with darker skin and with daily dosing. Resolution was not confirmed in some patients. Consider discontinuing VYLEESI if hyperpigmentation develops. (5.2)
- Nausea: Reported by 40% of patients who received up to 8 monthly doses, requiring anti-emetic therapy in 13% of patients and leading to premature discontinuation for 8% of patients. Improved for most patients with the second dose. Consider discontinuing VYLEESI or initiating anti-emetic therapy for persistent or severe nausea. (5.3)

6 ADVERSE REACTIONS

Most common adverse reactions (incidence > 4%) are nausea, flushing, injection site reactions, headache, and vomiting. (6.1)

To report SUSPECTED ADVERSE REACTIONS, contact Cosette Pharmaceuticals, Inc. at 1-800-922-1038 or FDA at 1-800-FDA-1088 or www.fda.gov/medwatch

7 DRUG INTERACTIONS

- VYLEESI may slow gastric emptying and impact absorption of concomitantly administered oral medications. (7.1)
- VYLEESI may significantly decrease the systemic exposure of orally-administered naltrexone; avoid use with orally administered naltrexone-containing products intended to treat alcohol or opioid addiction. (7.2)

8 USE IN SPECIFIC POPULATIONS

- Pregnancy: Advise patients to discontinue VYLEESI if pregnancy is suspected. (8.1)
- Females of Reproductive Potential: Advise patients to use effective contraception while taking VYLEESI. (8.3)

FULL PRESCRIBING INFORMATION

1 INDICATIONS AND USAGE

VYLEESI is indicated for the treatment of premenopausal women with acquired, generalized hypoactive sexual desire disorder (HSDD), as characterized by low sexual desire that causes marked distress or interpersonal difficulty and is NOT due to:

- A co-existing medical or psychiatric condition,
- Problems with the relationship, or
- The effects of a medication or drug substance.

Acquired HSDD refers to HSDD that develops in a patient who previously had no problems with sexual desire. Generalized HSDD refers to HSDD that occurs regardless of the type of stimulation, situation or partner.

Limitations of Use

- VYLEESI is not indicated for the treatment of HSDD in postmenopausal women or in men.
- VYLEESI is not indicated to enhance sexual performance.

2 DOSAGE AND ADMINISTRATION

2.1 Recommended Dosage

The recommended dosage of VYLEESI is 1.75 mg administered subcutaneously in the abdomen or thigh, as needed, at least 45 minutes before anticipated sexual activity. The duration of efficacy after each dose is unknown and the optimal window for VYLEESI administration has not been fully characterized. Patients may decide the optimal time for VYLEESI administration based on how they experience the duration of effect on desire and any adverse reactions such as nausea [see Warnings and Precautions (5.3)].

Patients should not administer more than one dose within 24 hours. The efficacy of consecutive doses within 24 hours has not been established and administering doses close together may increase the risk of additive effects on blood pressure [see Warnings and Precautions (5.1)].

Administering more than 8 doses per month is not recommended. Few patients in the phase 3 program received more than 8 doses per month. Also, more frequent dosing increases the risk for focal hyperpigmentation and the length of time per month when blood pressure is increased [see Warnings and Precautions (5.1, 5.2)].

VYLEESI is self-administered via a prefilled autoinjector pen. Visually inspect the drug product for particulate matter and discoloration prior to administration, whenever solution and container permit. Discard if the solution is cloudy, discolored, or visible particles are observed.

2.2 Discontinuation of VYLEESI

Discontinue VYLEESI after 8 weeks if the patient does not report an improvement in her symptoms.

3 DOSAGE FORMS AND STRENGTHS

Subcutaneous injection: 1.75 mg/0.3 mL clear solution in a single-dose autoinjector.

4 CONTRAINDICATIONS

VYLEESI is contraindicated in patients who have uncontrolled hypertension or known cardiovascular disease [see Warnings and Precautions (5.1)].

5 WARNINGS AND PRECAUTIONS

5.1 Transient Increase in Blood Pressure and Reduction in Heart Rate

VYLEESI transiently increases blood pressure and reduces heart rate after each dose. In clinical studies, VYLEESI induced maximal increases of 6 mmHg in systolic blood pressure (SBP) and 3 mmHg in diastolic blood pressure (DBP) that peaked between 2 to 4 hours post dose. There was a corresponding reduction in heart rate up to 5 beats per minute. Blood pressure and heart rate returned to baseline usually within 12 hours post-dose. No additive effects were seen for blood pressure or heart rate following repeat daily dosing 24-hours apart for up to 16 days [see Clinical Pharmacology (12.2)].

Before initiating VYLEESI, and periodically during treatment, consider the patient's cardiovascular risk and ensure blood pressure is well-controlled. VYLEESI is not recommended for patients at high risk for cardiovascular disease and is contraindicated in patients with uncontrolled hypertension or known cardiovascular disease [ see Contraindications (4)].

To minimize the risk of more pronounced blood pressure effects, advise patients to not take more than one VYLEESI dose within 24 hours [see Dosage and Administration (2.1)].

5.2 Focal Hyperpigmentation

In the phase 3 placebo-controlled trials, focal hyperpigmentation, including involvement of the face, gingiva, and breasts, was reported in 1% of patients who received up to 8 doses per month of VYLEESI compared to no placebo-treated patients. In another clinical study, 38% of patients developed focal hyperpigmentation after receiving VYLEESI daily for 8 days; among patients who continued VYLEESI for 8 more consecutive days, an additional 14% developed new focal pigmentary changes. Patients with dark skin were more likely to develop focal hyperpigmentation. Resolution of the focal hyperpigmentation was not confirmed in all patients after discontinuation of VYLEESI. More than 8 monthly doses of VYLEESI is not recommended. Consider discontinuing VYLEESI if hyperpigmentation develops.

5.3 Nausea

In the phase 3 placebo-controlled trials, nausea was the most commonly reported adverse reaction, reported in 40% of VYLEESI-treated patients, requiring anti-emetic therapy in 13% of VYLEESI-treated patients and leading to premature discontinuation from the trials for 8% of VYLEESI-treated patients. Nausea improves for most patients with the second dose [see Adverse Reactions (6.1)] . Consider discontinuing VYLEESI for persistent or severe nausea or initiating anti-emetic therapy for those patients who are bothered by nausea but wish to continue with VYLEESI treatment.

6 ADVERSE REACTIONS

The following adverse reactions are discussed in greater detail elsewhere in labeling:

- Transient increases in blood pressure and reductions in heart rate [see Warnings and Precautions (5.1) and Clinical Pharmacology (12.2) ]
- Focal hyperpigmentation [see Warnings and Precautions (5.2)]
- Nausea [see Warnings and Precautions (5.3) ]

6.1 Clinical Trials Experience

Because clinical trials are conducted under widely varying conditions, adverse reaction rates observed in the clinical trials of a drug cannot be directly compared to the rates in the clinical trials of another drug and may not reflect the rates observed in practice.

The efficacy and safety of VYLEESI was studied in two identical, 24-week, randomized, double-blind, placebo-controlled trials in 1247 premenopausal women with acquired, generalized HSDD. The age range was 19-56 years old with a mean age of 39 years old; 86% were White and 12% were Black. Both trials also included a 52-week open-label, uncontrolled extension phase during which 684 patients received VYLEESI [see Clinical Studies (14)]. Most patients used VYLEESI two to three times per month and no more than once a week.

Serious adverse reactions were reported in 1.1% of VYLEESI-treated patients and 0.5% of placebo-treated patients.

Adverse Reactions Leading to Study Discontinuation

The discontinuation rate due to adverse reactions was 18% among patients treated with VYLEESI and 2% among patients treated with placebo. The most common adverse reactions leading to study drug discontinuation in the VYLEESI group were nausea (8%), headache (2%), vomiting (1%), flushing (1%), injection site reactions (1%), flu-like symptoms (<1%) and increased blood pressure (<1%).

Common Adverse Reactions

Table 1 provides the incidence of common adverse reactions (those reported in at least 2% of patients in the VYLEESI treatment group and at an incidence that was greater than in the placebo group). The most common adverse reactions included nausea, flushing, injection site reactions and headache. The majority of events were reported to be mild (31%) to moderate (40%) in intensity and transient.

Table 1: Adverse Reactions Occurring in ≥ 2% of Patients in Randomized, Double-Blind Controlled Trials with VYLEESI in Premenopausal Women with HSDD
 | VYLEESI (n = 627) % | Placebo (n= 620) %
Nausea | 40.0 | 1.3
Flushing | 20.3 | 0.3
Injection site reactionsa | 13.2 | 8.4
Headache | 11.3 | 1.9
Vomiting | 4.8 | 0.2
Cough | 3.3 | 1.3
Fatigue | 3.2 | 0.5
Hot flush | 2.7 | 0.2
Paraesthesia | 2.6 | 0.0
Dizziness | 2.2 | 0.5
Nasal congestion | 2.1 | 0.5
aIncludes injection site pain, unspecified injection site reactions, erythema, hematoma, pruritus, hemorrhage, bruising, paresthesia and hypoesthesia

Nausea

In the pooled phase 3 placebo-controlled trials, nausea was the most common adverse reaction, reported in 40% of VYLEESI-treated patients compared to 1% of placebo-treated patients. The median onset of nausea was within one-hour post-dose and lasted about two hours in duration. The incidence of nausea was highest after the first VYLEESI dose (reported in 21% of patients) then declined to about 3% after subsequent doses. Thirteen percent of VYLEESI-treated patients received an anti-emetic medication. Overall, 8% of VYLEESI-treated patients and no placebo-treated patients prematurely discontinued the trials due to nausea. [see Warnings and Precautions (5.3)]

In a phase 4, single-dose, placebo-controlled clinical study, pre-treatment with oral ondansetron (a 5-HT3 receptor antagonist) did not reduce the incidence of nausea associated with VYLEESI treatment. In this study, 228 healthy women were randomized (1:1) to receive 8 mg ondansetron or placebo orally 30 minutes prior to a single administration of 1.75 mg of VYLEESI given subcutaneously. No significant difference in the incidence of VYLEESI-associated nausea was seen between the treatment groups. Therefore, pre-treatment with oral ondansetron given 30 minutes prior to VYLEESI administration does not reduce the incidence of VYLEESI-associated nausea and is not recommended. Treatment with ondansetron after VYLEESI administration or after the onset of nausea has not been formally studied.

Headache

In the pooled phase 3 placebo-controlled trials, headache occurred at a higher incidence in VYLEESI-treated patients (11%) than placebo-treated patients (2%). One patient experienced a headache event that was serious (intractable pain leading to hospitalization) and 1% of patients who received VYLEESI discontinued the study due to headache.

Flushing

In the pooled phase 3 placebo-controlled trials, flushing occurred more frequently in VYLEESI-treated patients (20%) than placebo-treated patients (<1%). None of the flushing events were serious and few were severe (<1%), and 1% of patients who received VYLEESI discontinued the study due to flushing.

Less Common Adverse Reactions

Less common adverse reactions occurring in <2% of VYLEESI-treated patients and at an incidence greater than in the placebo group were upper abdominal pain, diarrhea, myalgia, arthralgia, pain, restless leg syndrome, rhinorrhea, increased creatine phosphokinase, blood pressure increased, pain in extremity and focal skin hyperpigmentation.

Acute hepatitis

In the open-label, uncontrolled extension phase of one study, a single case of acute hepatitis was reported in a patient who had received 10 doses of VYLEESI over one year. She presented with serum transaminases exceeding 40 times the upper limit of normal (ULN), total bilirubin 6 times the ULN, and alkaline phosphatase less than 2 times ULN. Liver tests returned to normal 4 months after study drug discontinuation. Because another etiology was not identified, the role of VYLEESI could not definitively be excluded. There was no imbalance between treatment groups in serum transaminase outliers or other signals for hepatotoxicity in the clinical development program.

7 DRUG INTERACTIONS

7.1 Effect of VYLEESI on Other Drugs

VYLEESI may slow gastric emptying and thus has the potential to reduce the rate and extent of absorption of concomitantly administered oral medications. Instruct patients to avoid the use of VYLEESI when taking concomitant oral drugs that are dependent on threshold concentrations for efficacy (e.g., antibiotics). In addition, patients should consider discontinuing VYLEESI if there is a delayed drug effect of concomitant oral medications when a quick onset of drug effect is desired (e.g. drugs for pain relief such as indomethacin).

7.2 Naltrexone

As VYLEESI may significantly decrease the systemic exposure of orally-administered naltrexone, patients should avoid using VYLEESI with an orally administered naltrexone-containing product that is intended to treat alcohol and opioid addiction due to the severe consequence of naltrexone treatment failure [see Clinical Pharmacology (12.3)].

8 USE IN SPECIFIC POPULATIONS

8.1 Pregnancy

Pregnancy Exposure Registry

There will be a pregnancy exposure registry that monitors pregnancy outcomes in women exposed to VYLEESI during pregnancy. Pregnant women exposed to VYLEESI and healthcare providers are encouraged to call the VYLEESI Pregnancy Exposure Registry at (800) 922-1038.

Risk Summary

The few pregnancies in women exposed to VYLEESI in clinical trials are insufficient for determining whether there is a drug-associated risk for major birth defects, miscarriage or adverse maternal or fetal outcomes.

Based on findings in animal studies, the use of VYLEESI in pregnant women may be associated with the potential for fetal harm. In animal reproduction and development studies, daily subcutaneous administration of bremelanotide to pregnant dogs during the period of organogenesis at exposures greater than or equal to 16 times the maximum recommended dose (based on area under the concentration-time curve or AUC) produced fetal harm. In mice subcutaneously dosed with bremelanotide during pregnancy and lactation, developmental effects were observed in the offspring at greater than or equal to 125-times the maximum recommended dose (based on AUC) [see Data]. However, the lowest bremelanotide dose associated with fetal harm has not been identified for either species. For this reason, women should use effective contraception while taking VYLEESI and discontinue VYLEESI if pregnancy is suspected.

In the U.S. general population, the estimated background risk of major birth defects and miscarriage in clinically recognized pregnancies is 2% to 4% and 15% to 20%, respectively.

Data

Human Data

There were 7 pregnancies reported in the clinical trials of more than 1057 patients treated with VYLEESI for up to 12 months. Among these 7 pregnancies, no major congenital anomalies were reported. There was one spontaneous abortion (miscarriage), five full-term live births, and one outcome was unknown due to loss to follow-up.

Animal Data

An embryofetal development study was conducted in the dog and a pre- and postnatal development study was conducted in the mouse to inform developmental risk. These two species are not routinely used for reproductive toxicity assessment but were the only two species that could be successfully dosed by the subcutaneous route during gestation.

Bremelanotide was administered subcutaneously to pregnant dogs (8/dose) at 2, 8, or 20 mg/kg from gestation day (GD) 18-35, corresponding to the period from implantation to late embryogenesis in the dog. Embryofetal toxicity, as measured by post-implantation loss, was elevated approximately 3 to 8-fold compared to controls across all treated groups but was not dose-dependent. A developmental no-observed-effect level (NOEL) was not set. At the low dose of 2 mg/kg/day in the dog, exposure was approximately 16 times the human exposure based on AUC.

In a pre- and postnatal development study, female mice (30/dose) were dosed subcutaneously at 0, 30, 75, and 150 mg/kg/day from GD 6 through lactation day (LD) 28, and two generations of offspring were assessed (F1 and F2). There were no effects on reproductive parameters in parental (F0) or F1 generation animals at doses up to 150 mg/kg/day (approximately 760 times the human AUC). However, developmental delays were observed in the F1 generation mice at ≥ 30 mg/kg/day (approximately 125 times the human AUC). For that reason, a developmental NOEL was not set. There were no significant effects on the growth and development of F2 generation pups.

8.2 Lactation

Risk Summary

There is no information on the presence of bremelanotide or its metabolites in human milk, the effects on the breastfed infant, or the effects on milk production.

The developmental and health benefits of breastfeeding should be considered along with the mother's clinical need for VYLEESI and any potential adverse effects on the breastfed child from VYLEESI or from the underlying maternal condition.

8.3 Females and Males of Reproductive Potential

Contraception

Use of VYLEESI during pregnancy is not recommended [see Use in Specific Populations (8.1)]. Advise females of reproductive potential to use effective contraception while taking VYLEESI, and to discontinue VYLEESI if pregnancy is suspected.

8.4 Pediatric Use

The safety and effectiveness of VYLEESI have not been established in pediatric patients.

8.5 Geriatric Use

The safety and effectiveness of VYLEESI have not been established in geriatric patients.

8.6 Renal Impairment

No dosing adjustments are recommended for patients with mild to moderate (eGFR 30-89 mL/min/1.73 m^2) renal impairment. Use with caution in patients with severe (eGFR <30 mL/min/1.73 m^2) renal impairment, because these patients may have an increase in the incidence and severity of adverse reactions (e.g., nausea and vomiting) [see Clinical Pharmacology (12.3)] .

8.7 Hepatic Impairment

No dosing adjustments are recommended for patients with mild to moderate (Child-Pugh A and B; score 5-9) hepatic impairment. VYLEESI has not been evaluated in patients with severe hepatic impairment. Use with caution in patients with severe (Child-Pugh C; score 10-15) hepatic impairment, because these patients may have an increase in the incidence and severity of adverse reactions (e.g., nausea and vomiting) [see Clinical Pharmacology (12.3)].

10 OVERDOSAGE

No reports of overdosage with VYLEESI have been reported. Nausea, focal hyperpigmentation and more pronounced blood pressure increases are more likely with higher doses. In the event of overdosage, treatment should address the symptoms with supportive measures, as needed.

11 DESCRIPTION

VYLEESI (bremelanotide injection) contains bremelanotide, a melanocortin receptor agonist for subcutaneous administration via an autoinjector. Bremelanotide acetate is a synthetic, cyclic heptapeptide with a free acid at the carboxyl terminus and an acetylated amino group at the amino terminus of the peptide with the following structure:

Ac-Nle-cyclo-(Asp-His-D-Phe-Arg-Trp-Lys-OH) ● xCH3COOH

The molecular formula of bremelanotide acetate is C50H68N14O10● xCH3COOH (1≤ x ≤ 2) and the molecular weight is 1025.2 (free base).

VYLEESI (bremelanotide injection) is supplied as a sterile, clear solution in a pre-filled syringe contained in a single-dose autoinjector for subcutaneous administration. Each pre-filled syringe contains 1.75 mg of bremelanotide (equivalent to 1.89 mg bremelanotide acetate) in 0.3 mL solution. Inactive ingredients consist of 2.5% glycerin, sterile water for injection, and hydrochloric acid or sodium hydroxide added to adjust the pH.

12 CLINICAL PHARMACOLOGY

12.1 Mechanism of Action

Bremelanotide is a melanocortin receptor (MCR) agonist that nonselectively activates several receptor subtypes with the following order of potency: MC1R, MC4R, MC3R, MC5R, MC2R. At therapeutic dose levels, binding to MC1R and MC4R is most relevant. Neurons expressing MC4R are present in many areas of the central nervous system (CNS). The mechanism by which VYLEESI improves HSDD in women is unknown. The MC1R is expressed on melanocytes; binding at this receptor leads to melanin expression and increased pigmentation.

12.2 Pharmacodynamics

Transient Increases in Blood Pressure

In an open-label ambulatory blood pressure monitoring study of 127 premenopausal women receiving VYLEESI once daily, there was a mean increase of 1.9 mmHg (95% CI: 1.0 to 2.7) in daytime systolic blood pressure (SBP) and a mean increase of 1.7 mmHg (95% CI: 0.9 to 2.4) in daytime diastolic blood pressure (DBP) after 8 days of dosing. The increase in SBP and DBP was transient with a mean peak effect in SBP of 2.8 mmHg between 4 to 8 hours post-dose and 2.7 mmHg for DBP at 0 to 4 hours post-dose. The increase in BP after 8 days of dosing was accompanied by a simultaneous and transient mean decrease in heart rate of 0.5 beats per minute (95% CI: -1.6 to -0.7). The SBP and DBP values 12 to 24-hours post-dose were similar to the pre-dose values [see Warnings and Precautions (5.1)].

Alcohol Interaction

A placebo-controlled, randomized, double-blind, three-period, three-way crossover study was conducted to assess the safety of a single intranasal 20 mg dose of bremelanotide co-administered with alcohol in 12 healthy male and 12 healthy female subjects. Intranasal bremelanotide or placebo spray was administered 10 minutes after consumption of placebo drink or 0.6 g/kg ethanol (equivalent of three 12 ounce cans of beer containing 5% alcohol content, three 5 ounce glasses of wine containing 12% alcohol content, or three 1.5 ounce shots of 80-proof spirit in a 70 kg person).

The 20 mg intranasal dose achieves a 2.5-fold higher mean Cmax than that of VYLEESI. Alcohol consumption had no effect on the pharmacokinetic profile of bremelanotide. The incidence of flushing was higher with bremelanotide plus ethanol compared to ethanol alone, but similar to the incidence with bremelanotide alone. The incidence of headache was higher with bremelanotide plus ethanol compared to bremelanotide alone, but similar to the incidence with ethanol alone. The incidence of other adverse reactions was similar across the treatment groups. The incidence of abnormal orthostatic blood pressure reductions was comparable between the bremelanotide plus ethanol group and the ethanol alone group. No participants discontinued due to adverse reactions.

Cardiac Electrophysiology

A 20 mg intranasal dose of bremelanotide does not prolong the QTc interval to any clinically relevant extent.

12.3 Pharmacokinetics

Following subcutaneous administration of VYLEESI, the mean plasma Cmax and AUC of bremelanotide are 72.8 ng/mL and 276 hr*ng/mL, respectively. Mean plasma concentrations of bremelanotide increase in a less than dose proportional manner in the dose range of 0.3 to 10 mg, with mean Cmax levels reaching a plateau at the 7.5 mg subcutaneous dose level (approximately 4.3 times the maximum recommended dose).

Absorption

Bremelanotide median Tmax is approximately 1.0 hour (range: 0.5 - 1.0 hours) in plasma. The absolute bioavailability of bremelanotide following subcutaneous administration of VYLEESI was about 100%. The site of subcutaneous administration (abdomen and thigh) had no significant effect on the systemic exposure to bremelanotide.

Distribution

Twenty-one percent of bremelanotide binds to human serum protein. The mean (SD) volume of distribution after a single subcutaneous administration of VYLEESI is 25.0 ± 5.8 L.

Elimination

Following a single subcutaneous administration of VYLEESI, mean terminal half-life of bremelanotide is approximately 2.7 hours (range: 1.9– 4.0 hours) and the mean (± SD) clearance (CL/F) is 6.5 ±1.0 L/hr.

Metabolism

As a peptide with 7 amino acids, the primary metabolic pathway of bremelanotide involves multiple hydrolyses of the amide bond of the cyclic peptide.

Excretion

Following administration of a radiolabeled dose, 64.8% of the total radioactivity was recovered in urine and 22.8% in feces.

Specific Populations

Patients with Renal Impairment

Following a single subcutaneous dose of VYLEESI, bremelanotide exposure (AUC) increased 1.2-fold in patients with mild (eGFR, 60 to 89 mL/min/1.73 m^2) renal impairment, 1.5-fold in patients with moderate (eGFR, 30 to 59 mL/min/1.73 m^2) renal impairment, and 2-fold in patients with severe (eGFR, <30 mL/min/1.73 m^2) renal impairment [see Use in Specific Populations (8.6)] .

Patients with Hepatic Impairment

Following a single subcutaneous dose of VYLEESI, bremelanotide exposure (AUC0-inf) increased 1.2-fold in patients with mild (Child-Pugh A; score of 5-6) hepatic impairment and 1.7-fold in patients with moderate (Child-Pugh B; score of 7-9) hepatic impairment [see Use in Specific Populations(8.7)]. The effect of severe hepatic impairment on the pharmacokinetics of bremelanotide was not studied.

Drug Interaction Studies

Potential for VYLEESI to Influence the Pharmacokinetics of Other Drugs

VYLEESI may reduce the rate and extent of absorption of concomitantly administered oral medications, likely due to slowing gastric motility. In clinical pharmacology studies, VYLEESI did not affect the absorption of the tested orally administered concomitant medications to any clinically relevant degree, except for naltrexone and indomethacin [see Drug Interactions (7)].

The effects of bremelanotide on the pharmacokinetics of other drugs are summarized below as change relative to the other drug administered alone (test/reference) (Figure 1).

Figure 1: Effects of Bremelanotide 1.75 mg SC on the Pharmacokinetic Exposures of Orally Administered Medications

Note: AUC = area under the plasma concentration-time curve; BMT = bremelanotide; CI = confidence interval; Cmax= maximum plasma concentration; SC = subcutaneous.

13 NONCLINICAL TOXICOLOGY

13.1 Carcinogenesis, Mutagenesis, Impairment of Fertility

Carcinogenesis

There were no significant increases in tumor incidence in two-year carcinogenicity studies with intranasal administration (0.5, 2.5, and 5 mg/animal/day) of bremelanotide to male and female rats, and subcutaneous administration (3, 9, and 15 mg/kg/day) to male and female mice. Multiples of exposure were calculated based on average Cmax at the high dose over the course of the study and were 1.1-fold and 111-fold the human Cmax for rats and mice, respectively.

Mutagenesis

Bremelanotide was not genotoxic or mutagenic in a battery of tests, including the in vitro bacterial reverse mutation assay, the in vitro chromosomal aberration test in Chinese Hamster Ovary cells, and the in vivo mouse micronucleus assay.

Impairment of Fertility

There were no effects on fertility in male (75 mg/kg/day, approximately 375 times the human AUC) or female (150 mg/kg/day, approximately 760 times the human AUC) mice following subcutaneous administration.

14 CLINICAL STUDIES

The efficacy of VYLEESI for the treatment of HSDD in premenopausal women was evaluated in two identical, Phase 3, randomized, double-blind, placebo-controlled trials: NCT02333071and NCT02338960(Study 1 and Study 2). Both trials included premenopausal women with acquired, generalized HSDD of at least 6 months' duration. All patients in heterosexual relationships were required to use an effective form of contraception. A majority of patients (74% in Study 1 and 67% in Study 2) reported HSDD with concomitant decreased arousal. The trials consisted of two phases: a Core Study Phase (24-week placebo-controlled, double-blind treatment period) and an uncontrolled, 52-week Open-label Extension Study Phase.

Study participants were randomized to subcutaneous injections of VYLEESI 1.75 mg (n= 635) or placebo (n= 632), self-administered by an autoinjector on an as-needed basis. Patients were instructed to administer the drug approximately 45 minutes prior to anticipated sexual activity. Patients were not to administer more than one dose within a 24-hour period and no more than twelve doses per month. Trial participants were mostly Caucasian (86%) or Black (12%). The mean age of study participants was 39 years old (range 19 to 56 years old); the mean duration in a monogamous relationship was 12 years, and the mean duration of HSDD was approximately 4 years. Across the two trials, the median number of VYLEESI injections was 10 in the 24-week double-blind treatment period and 12 during the uncontrolled open-label extension. Most patients used VYLEESI two to three times per month and no more than once a week.

Study 1 and Study 2 had the following co-primary efficacy endpoints:

- Change from baseline to end of study (EOS) in the Desire domain from the Female Sexual Function Index (FSFI) (Questions 1 and 2). Question 1 asks patients “Over the past 4 weeks, how often did you feel sexual desire or interest?”, with responses ranging from 1 (almost never or never) to 5 (almost always or always). Question 2 asks patients “Over the past 4 weeks, how would you rate your level (degree) of sexual desire or interest?”, with responses ranging from 1 (very low or none at all) to 5 (very high). The FSFI Desire domain score was calculated by adding the patient's responses to these two questions then multiplying that sum by 0.6. The FSFI Desire Domain score ranged from 1.2 to 6. An increase in the FSFI Desire domain score over time denotes improvement in sexual desire.
- Change from baseline to EOS in the score for feeling bothered by low sexual desire as measured by the Female Sexual Distress Scale – Desire/Arousal/Orgasm Question 13 (FSDS-DAO Q13). This question asks patients, “How often did you feel: Bothered by low sexual desire?” Patients assessed their sexual distress over a 30-day recall period and responded on a scale of 0 (never) to 4 (always). A decrease in the FSDS-DAO Q13 score over time denotes improvement in the level of distress associated with low sexual desire.

EOS is defined as the patient's last study visit during the double-blind treatment period. For patients who completed the double-blind treatment period, the EOS visit occurred at Week 24.

Efficacy results for these co-primary endpoints from Study 1 and Study 2 are summarized in Table 2and Table 3. In both studies, VYLEESI showed a statistically significant increase in the FSFI Desire Domain score and a statistically significant decrease in the FSDS-DAO Q13 score from baseline to the EOS visit compared to placebo. The magnitude of the treatment differences was similar in both studies.

Table 2: Efficacy Results for the FSFI-Desire Domain Score in Premenopausal HSDD Patients in Study 1 and Study 2 (MITT* Population)
 | Study 1 |  | Study 2
 | VYLEESI 1.75 mg (N= 313) | Placebo (N= 315) | VYLEESI 1.75 mg (N= 282) | Placebo (N=288)
Mean Baseline (SD)^1 | 2.1 (0.9) | 2.0 (0.8) | 2.0 (0.8) | 2.1 (0.8)
Mean Change from Baseline (SD) | 0.5 (1.1) | 0.2 (1.0) | 0.6 (1.0) | 0.2 (0.9)
Median Change from Baseline | 0.6 | 0 | 0.6 | 0
p-value^2 | 0.0002 |  | < 0.0001
^1 FSFI Desire score range: 1.2 to 6.0, with higher scores indicating greater desire.
^2 p-value from unadjusted Wilcoxon rank-sum test.
*MITT: modified intent to treat defined as all patients who were randomized, used at least one dose of double-blind study drug, and had at least one double-blind follow-up visit. However, one VYLEESI patient and one placebo patient in Study 1 and two placebo patients in Study 2 did not have either a baseline or EOS efficacy measurement and change from baseline could not be calculated. Therefore, N = the number of patients in the MITT population with an evaluable change measurement.

Table 3: Efficacy Results for the FSDS-DAO Q13 Score in Premenopausal HSDD Patients in Study 1 and Study 2 (MITT* Population)
 | Study 1 |  | Study 2
 | VYLEESI 1.75 mg (N= 313) | Placebo (N= 314) | VYLEESI 1.75 mg (N= 282) | Placebo (N=285)
Mean Baseline (SD)^1 | 2.9 (1.0) | 2.8 (0.9) | 2.9 (0.9) | 2.9 (0.9)
Mean Change from Baseline (SD) | -0.7 (1.2) | -0.4 (1.1) | -0.7 (1.1) | -0.4 (1.1)
Median Change from Baseline | -1 | 0 | -1 | 0
p- value^2 | < 0.0001 |  | 0.0053
^1 FSDS-DAO Q13 score range: 0 to 4, with higher scores indicating greater bother.
^2 p-value from unadjusted Wilcoxon rank-sum test
*MITT: modified intent to treat defined as all patients who were randomized, used at least one dose of the double-blind drug and had at least one double-blind follow-up visit. However, one VYLEESI patient and two placebo patients in Study 1 and five placebo patients in Study 2 did not have either a baseline or EOS efficacy measurement and change from baseline could not be calculated. Therefore, N = the number of patients in the MITT population with an evaluable change measurement.

Supplementary analyses were conducted to help interpret clinical meaningfulness of the observed score change from baseline to EOS in the FSFI-Desire Domain and FSDS-DAO Q13. These analyses defined responders for each coprimary efficacy endpoint by anchoring change from baseline to EOS with multiple anchor measures. Each anchor analysis considered responders to be those who reported experiencing meaningful change at their EOS visit according to the respective anchor measure.

Because a greater percentage of MITT patients in the VYLEESI group prematurely discontinued the 24-week double-blind treatment period compared to placebo patients (40% vs. 13% for Study 1 and 39% vs. 25% for Study 2), an exploratory analysis was performed examining the percentages of patients who were able to complete the treatment period and improved from baseline. Figure 2 displays the percentages of the MITT patients in the two Phase 3 trials who completed the 24-week double-blind treatment period and achieved various levels of increase in the FSFI-Desire Domain Score from baseline (higher scores indicate increased sexual desire). Figure 3 displays the percentages of the MITT patients in the two clinical trials who completed the 24-week double-blind treatment period and achieved various levels of reduction in the FSDS-DAO Q13 score from baseline (higher scores indicate greater reduction in distress).

Figure 2: Percent of Patients (MITT Population) who Completed the 24-Week Double-Blind Treatment Period and Achieved Various Levels of Increases in the FSFI-Desire Domain Score

Patients who did not complete the double-blind treatment period or were missing baseline scores are not considered to have experienced an increase in FSFI-Desire Domain score at the end of the double-blind treatment period.

Responder threshold: at least 1.2-point increase from baseline in FSFI-Desire Domain score. The threshold was defined for these studies by anchoring change from baseline to end of treatment with multiple anchor measures.

Figure 3: Percent of Patients (MITT Population) who Completed the 24-Week Double-Blind Treatment Period and Achieved Various Levels of Reductions in the FSDS-DAO Q13 Score

Patients who did not complete the double-blind treatment period or were missing change from baseline scores are not considered to have experienced a decrease in FSDS-DAO Q13 score at the end of the double-blind treatment period.

Responder threshold: at least 1-point decrease from baseline in the FSDS-DAO Q13 score. The threshold was defined for these studies by anchoring change from baseline to end of treatment with multiple anchor measures.

There was no significant difference between treatment groups in the change from baseline to end of study visit in the number of satisfying sexual events (SSEs), a secondary endpoint.

Efficacy results for the number of SSEs are summarized in Table 4.

Table 4: Efficacy Results for the Number of Satisfying Sexual Events in Premenopausal HSDD Patients in Study 1 and Study 2 (MITT* Population)
 | Study 1 |  | Study 2
 | VYLEESI 1.75 mg (N= 314) | Placebo (N= 316) | VYLEESI 1.75 mg (N= 282) | Placebo (N=290)
Mean Baseline (SD) | 0.7 (1.0) | 0.8 (1.1) | 0.8 (1.1) | 0.7 (1.0)
Mean Change from Baseline (SD) | 0.0 (1.4) | -0.1 (1.4) | 0.0 (1.3) | 0.0 (1.2)
Median Change from Baseline | 0 | 0 | 0 | 0
p- value^1 | 0.76 |  | 0.70
^1 p-value from unadjusted Wilcoxon rank-sum test.
*MITT: modified intent to treat defined as all patients who were randomized, used at least one dose of double-blind drug and had at least 1 double-blind follow-up visit. N = the number of patients in the MITT population.

16 HOW SUPPLIED / STORAGE AND HANDLING

VYLEESI (bremelanotide) is supplied as:

1.75 mg bremelanotide in 0.3 mL solution in a single-dose, disposable prefilled autoinjector (NDC 0713-0897-06) provided in a carton of 4 autoinjectors (NDC 0713-0897-04), carton of 2 autoinjectors (NDC 0713-0897-02).

Storage

Store at or below 25°C (77°F). Do not freeze. Protect from light.

17 PATIENT COUNSELING INFORMATION

Advise the patient to read the FDA-approved patient labeling (Patient Information and Instructions for Use).

Transient Increase in Blood Pressure and Decrease in Heart Rate

Advise patients that increases in blood pressure and decreases in heart rate may occur after taking each VYLEESI dose, and that these changes usually resolve within 12 hours post-dose [see Warnings and Precautions (5.1)].

Advise patients not to take VYLEESI within 24 hours of a prior dose and that more than 8 doses per month is not recommended. Advise patients that taking VYLEESI more frequently or too close together may lead to more pronounced increases in blood pressure [see Dosage and Administration (2.1)].

Focal Hyperpigmentation

Advise patients that focal hyperpigmentation, including on the face, gingiva and breasts, may occur when VYLEESI is used intermittently, particularly in patients with darker skin. The incidence may increase with daily VYLEESI use. Advise patients that the pigmentary changes may not resolve completely after stopping VYLEESI, and to contact their healthcare provider if they have any concerns about changes to their skin [see Warnings and Precautions (5.2)] .

Nausea

Advise patients that nausea may occur, most commonly with the first injection of VYLEESI, but could occur intermittently with continued use. Advise patients that nausea most commonly lasts for two hours after taking a dose but could last longer in some patients, and that anti-emetic medications may be necessary. Advise patients to contact their healthcare provider for persistent or severe nausea [see Warnings and Precautions(5.3)].

Females of Reproductive Potential

Advise patients to use effective contraception while taking VYLEESI and to discontinue VYLEESI if pregnancy is suspected. Advise pregnant patients that there is a pregnancy registry that monitors pregnancy outcomes in women exposed to VYLEESI during pregnancy [see Use in Specific Populations (8.1, 8.3)].

Marketed By:
Cosette Pharmaceuticals, Inc.
South Plainfield, NJ 07080

VYLEESI is a registered trademark of Cosette Pharmaceuticals, Inc.

© 2024 Cosette Pharmaceuticals, Inc. All rights reserved.

8-0897CP1
Rev. 03/2024

PATIENT INFORMATION
VYLEESI® (vahy-lee-see)
(bremelanotide injection)
for subcutaneous use

What is VYLEESI?
VYLEESI is a prescription medicine used to treat hypoactive (low) sexual desire disorder (HSDD) in women who have not gone through menopause, who have not had problems with low sexual desire in the past, and who have low sexual desire no matter the type of sexual activity, the situation, or the sexual partner. Women with HSDD have low sexual desire that is troubling to them. Their low sexual desire is not due to:

- a medical or mental health problem
- problems in the relationship
- medicine or other drug use

VYLEESI is not for the treatment of HSDD in women who have gone through menopause or in men.
VYLEESI is not for use to improve sexual performance.
VYLEESI is not for use in children.

Do not use VYLEESI if you have:

- high blood pressure that is not controlled (uncontrolled hypertension)
- known heart (cardiovascular) disease

Before using VYLEESI, tell your healthcare provider about all of your medical conditions, including if you:

- have high blood pressure.
- have heart problems.
- have kidney problems.
- have liver problems.
- are pregnant or plan to become pregnant. It is not known if VYLEESI will harm your unborn baby.
  - Pregnancy Registry:There will be a pregnancy registry for women who use VYLEESI during pregnancy. The purpose of this registry is to collect information about the health of you and your baby. Talk to your healthcare provider about how you can take part in this registry or call the VYLEESI Pregnancy Exposure Registry at 800-922-1038.
  - Women who can become pregnant should use effective birth control during treatment with VYLEESI. Talk to your healthcare provider about birth control choices that may be right for you during this time. Stop using VYLEESI and tell your healthcare provider right away if you become pregnant or think you might be pregnant during treatment with VYLEESI.
- are breastfeeding or plan to breastfeed. It is not known if VYLEESI passes into your breast milk. Talk with your healthcare provider about the best way to feed your baby if you use VYLEESI.

Tell your healthcare provider about all the medicines you take, including prescription and over-the-counter medicines, vitamins, and herbal supplements. VYLEESI may affect the way other medicines work, and other medicines may affect the way VYLEESI works.
Know the medicines you take. Keep a list of them to show your healthcare provider and pharmacist each time you get a new medicine.

How should I use VYLEESI?

See the detailed “ Instructions for Use” that comes with VYLEESI for information on how to prepare and inject a dose of VYLEESI .Talk to your healthcare provider or pharmacist if you have any questions.

- Use VYLEESI exactly as prescribed by your healthcare provider.
- VYLEESI comes in an autoinjector that you or your caregiver may use at home to give injections.
- VYLEESI is given as an injection under the skin (subcutaneous injection), in your thighs or stomach area (abdomen).
- Inject VYLEESI at least 45 minutes before you think that you will begin sexual activity.
- Do not inject more than 1 dose of VYLEESI within 24 hours of your last dose.
- Do not inject more than 8 doses of VYLEESI within a month.

Tell your healthcare provider if your symptoms of HSDD have not improved after you have used VYLEESI for 8 weeks.

What are the possible side effects of VYLEESI?

VYLEESI can cause serious side effects, including:

- Temporary increase in blood pressure and decrease in heart rate:An increase in blood pressure and decrease in heart rate can happen shortly after you inject VYLEESI. These changes usually go away within 12 hours after your injection. Increases in blood pressure and an increased risk of heart (cardiovascular) problems can happen if you use VYLEESI more often than prescribed by your healthcare provider. See “How should I use VYLEESI?”
- Darkening of the skin on certain parts of the body (focal hyperpigmentation) including the face, gums (gingiva) and breast.The chance of darkening of the skin is increased in people with darker skin color. The chance of darkening of the skin is higher if VYLEESI is used every day. Darkening of the skin may not go away, even after you stop using VYLEESI. Tell your healthcare provider if you have any concerns about changes to your skin.

- Nausea. Nausea is common and can also be severe. Nausea most commonly happens after the first VYLEESI injection but can also happen after any dose of VYLEESI. The nausea usually lasts for about 2 hours but can last longer in some people. The nausea usually goes away by itself. Tell your healthcare provider if you have nausea that is severe or does not go away. Pre-treatment with the anti-nausea medicine ondansetron was not found to be effective to inhibit or reduce the nausea and is not recommended. Your healthcare provider may prescribe anti-nausea medicine for you to take after nausea occurs.

The most common side effects of VYLEESI include:

- flushing
- vomiting
- hot flush
- nasal congestion

- injection site reactions
- cough
- tingling

- headache
- fatigue
- dizziness

These are not all the possible side effects of VYLEESI.
Call your doctor for medical advice about side effects. You may report side effects to FDA at 1-800-FDA-1088.

How should I store VYLEESI?

- Store at or below 77°F (25°C).
- Do not freeze.
- Protect from light.

Keep VYLEESI and all medicines out of the reach of children.

General information about the safe and effective use of VYLEESI.
Medicines are sometimes prescribed for purposes other than those listed in a Patient Information leaflet. Do not use VYLEESI for a condition for which it was not prescribed. Do not give VYLEESI to other people, even if they have the same symptoms you have. It may harm them.
You can ask your healthcare provider or pharmacist for information about VYLEESI that is written for health professionals.

What are the ingredients in VYLEESI?
Active ingredient: bremelanotide
Inactive ingredients: 2.5% glycerin, sterile water for injection, and hydrochloric acid or sodium hydroxide is added to adjust the pH
Marketed By: Cosette Pharmaceuticals, Inc.
VYLEESI is a registered trademark of Cosette Pharmaceuticals, Inc.
©2024 Cosette Pharmaceuticals, Inc. All rights reserved.
For more information, go to www.VYLEESI.com or call Cosette Pharmaceuticals, Inc. Customer Service at the toll-free number 1-800-922-1038.

This Patient Information has been approved by the U.S. Food and Drug Administration

Revised: 03/2024

Instructions for Use | Read this Instructions for Use before you use VYLEESI and each time you get a refill. There may be new information. This information does not take the place of talking to your healthcare provider about your medical condition or treatment. Do not inject VYLEESI unless you have been trained by your healthcare provider. Talk to your healthcare provider or pharmacist if you have any questions.

 |  | Important Information | - Do not use more than 1 dose of VYLEESI in 24 hours. - Do not use more than 8 doses of VYLEESI within a month. - Use 1 autoinjector for your dose of VYLEESI.Throw away (dispose of) the autoinjector after giving your injection. See Step 6: Throw away (dispose of) the VYLEESI autoinjector. - Inject VYLEESI into the skin of the stomach area (abdomen) or thigh only. - Do not pull off the clear cap from the VYLEESI autoinjector until you are ready to inject VYLEESI.
 |  | Storage | Store at or below 77°F (25°C). Do not freeze. Protect from light. Keep VYLEESI and all medicines out of the reach of children.
Instructions for Use | Read this Instructions for Use before you use VYLEESI and each time you get a refill. There may be new information. This information does not take the place of talking to your healthcare provider about your medical condition or treatment. Do not inject VYLEESI unless you have been trained by your healthcare provider. Talk to your healthcare provider or pharmacist if you have any questions. | Supplies Needed for Your Injection: | - 1 alcohol wipe (not included in carton) - 1 VYLEESI autoinjector - 1 cotton ball or gauze (not included in carton) - 1 adhesive bandage (not included in carton) - 1 sharps disposal container for VYLEESI autoinjector disposal. See Step 6: Throw away (dispose of) the VYLEESI autoinjector.
 |  |  | Read and follow Step 1 to Step 6 to use the VYLEESI autoinjector.
 | Check the label on the autoinjector for the expiration date (EXP). Do not use the autoinjector if the expiration date has passed. Check the view window. You should see the gray tip in half of the view window and the medicine in half of the view window. If the view window is purple, the autoinjector will not work. Use a new autoinjector if the view window is purple. Look at the medicine in the view window. It should be clear and free of particles. Do not use if the medicine is cloudy, discolored, or contains particles. |  | The autoinjector must be used right away after it is activated.; Pull the clear cap from the autoinjector (See Figure A) to activate.; - Do not try to recap the autoinjector. - The autoinjector should be used or thrown away right after the cap is removed. See Step 6: Throw away (dispose of) the VYLEESI autoinjector.; Important :During the injection you will hear two clicks.; Place the purple tipflat against the center of the clean skin at your injection site.; Make sure you can see the view window (See Figure B).
 | Check that the clear cap fits tightly on the purple tip of the autoinjector. If the cap does not fit tightly or is damaged, do not use the autoinjector. Call Cosette Pharmaceuticals,Inc. at 1-800-922-1038.
 | Wash your hands with soap and water. Choose an injection site on your stomach area (abdomen) or the front of your thigh. Avoid the area on your abdomen that is 2 inches around your belly button (navel).; - Do not inject into skin that is irritated, sore, bruised, red, hard, or scarred. - Do not inject through your clothes. - Choose a different site each time you give yourself an injection. |  | Press down and hold the autoinjector firmly against your skin (See Figure C). You will hear the 1 stclick right away, which tells you that your injection has started. In about 2 seconds, you will hear a 2 ndclick. Continue to press and holdthe autoinjector firmly against your skin for about 5 secondsafter the 2nd click to be sure your injection is complete (See Figure D).
 | Clean the injection site with an alcohol wipe. Let the injection site air dry. Do not fan or blow on the clean area. Do not touch the injection site again before giving the injection.
 | Check that the view window is now purple with a small part of the gray tip still showing. This means that all of the medicine was given (See Figure E). Remove the autoinjector by lifting it straight off of your skin. After you remove the autoinjector from your skin, the purple tip will lock over the needle. |  | Put your used VYLEESI autoinjector in a FDA-cleared sharps disposal container right after use (See Figure F). Do not throw away (dispose of) the autoinjector in your household trash. If you do not have a FDA-cleared sharps disposal container, you may use a household container that is:; - made of heavy-duty plastic, - can be closed with a tight-fitting, puncture-resistant lid, without sharps being able to come out, - upright and stable during use, - leak-resistant, and - properly labeled to warn of hazardous waste inside the container.
 | - A cotton ball or gauze can be used initially to apply pressure after the injection if there is bleeding. An adhesive bandage should be applied after this, if needed. - Apply an adhesive bandage if needed. - Do not rub the injection site. |  | When your sharps disposal container is almost full, you will need to follow your community guidelines for the right way to dispose of your sharps disposal container. There may be state or local laws about how you should throw away used needles and syringes. For more information about safe sharps disposal and for specific information about sharps disposal in the state that you live in, go to the FDA's website at: http://www.fda.gov/safesharpsdisposal. Do not dispose of your used sharps disposal container in your household trash unless your community guidelines permit this. Do not recycle your used sharps disposal container. This Instructions for Use has been approved by the U.S. Food and Drug Administration.

Principal Display Panel – 4 Syringe Carton Label

NDC 0713- 0897-04

Rx ONLY

vyleesi®

(bremelanotide injection)

1.75 mg/0.3 mL | for subcutaneous use only

Principal Display Panel – Syringe Label

vyleesi®

(bremelanotide injection)